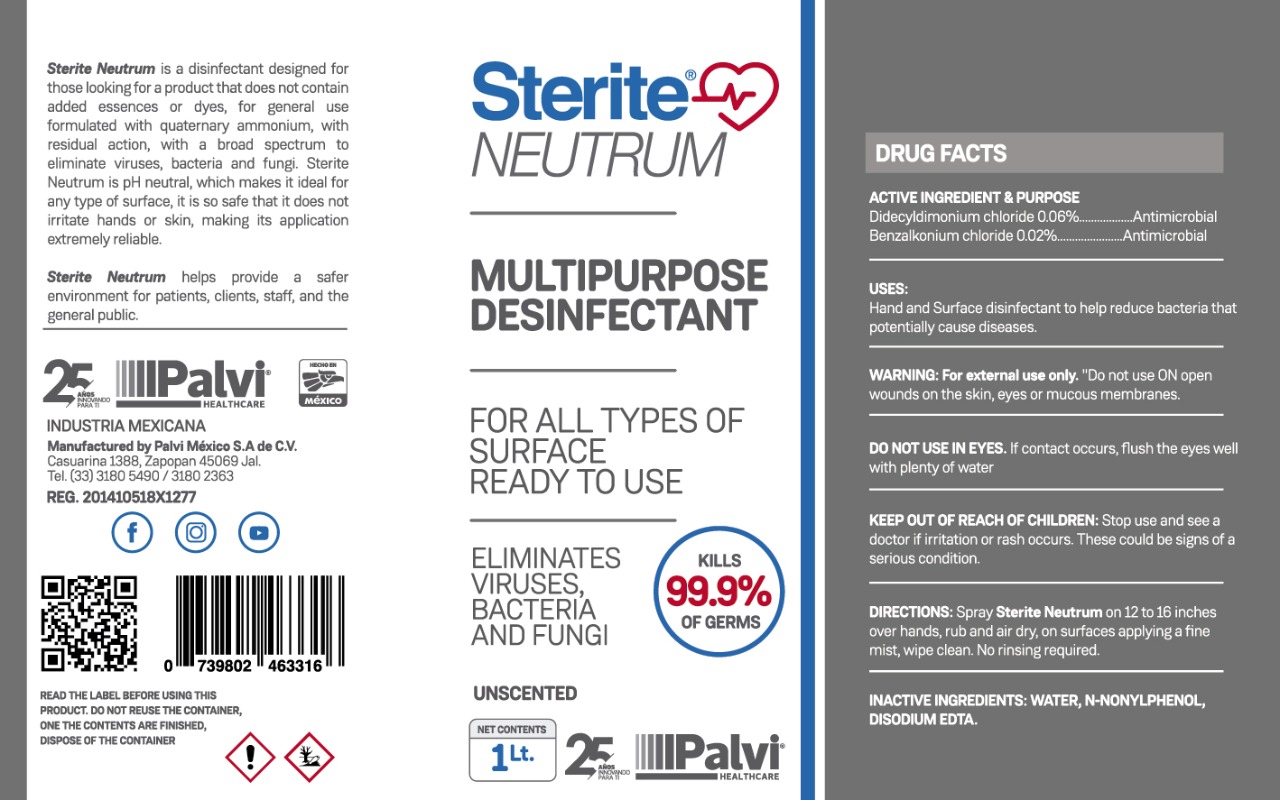 DRUG LABEL: STERITE NEUTRUM
NDC: 81576-3000 | Form: LIQUID
Manufacturer: PALVI MEXICO, S.A. DE C.V.
Category: otc | Type: HUMAN OTC DRUG LABEL
Date: 20210216

ACTIVE INGREDIENTS: BENZALKONIUM CHLORIDE 0.002 mg/1 mL; DIDECYLDIMONIUM CHLORIDE 0.006 mg/1 mL
INACTIVE INGREDIENTS: WATER 0.985 mL/1 mL; EDETATE DISODIUM 0.001 mL/1 mL; N-NONYLPHENOL (MIXED ISOMERS) 0.006 mL/1 mL

STERITE NEUTRUM SANITIZER

ACTIVE INGREDIENTS

DIDECYLDIMONIUM CHLORIDE

BENZALKONIUM CHLORIDE

PURPOSE

ANTIMICROBIAL

INDICATIONS AND USAGE

USES

HAND AND SURFACE DISINFECTANT TO HELP REDUCE BACTERIA THAT POTENTIALLY CAUSE DISEASES

DOSAGE AND ADMINISTRATION

DIRECTIONS SPRAY STERITE NEUTRUM ON 12 TO 16 INCHES OVER HANDS, RUB AND AIR DRY, ON SURFACES APPLYING A FINE MIST, WIPE CLEAN. NO RINSING REQUIRED.

WARNINGS

WARNING FOR EXTERNAL USE ONLY

WARNINGS AND PRECAUTIONS SECTION

DO NOT USE ON OPEN WOUNDS ON THE SKIN, EYES OR MUCOUS MEMBRANES

DO NOT USE IN EYES. IF CONTACT OCCURS, FLUSH THE EYES WELL WITH PLENTY OF WATER.

KEEP OUT OF REACH OF CHILDREN

STOP USE SECTION

STOP USE AND SEE A DOCTOR IF IRRITATION OR RASH OCCURS

THESE COULD BE SIGNS OF A SERIOUS CONDITION

INACTIVE INGREDIENT SECTION

INACTIVE INGREDIENTS: WATER, N-NONYLPHENOL, EUCALYPTOL, DISODIUM EDTA,